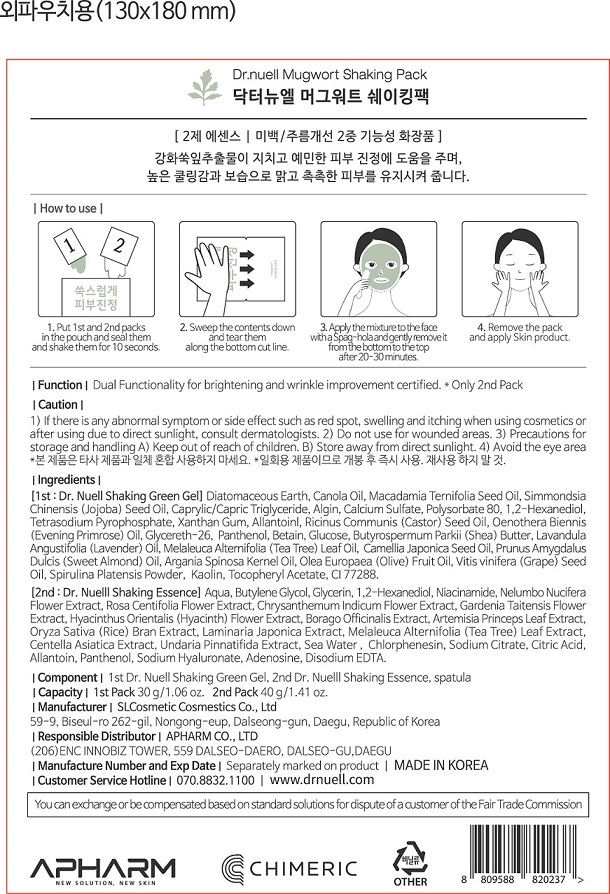 DRUG LABEL: Dr.NUELL Mugwort Shaking Pack
NDC: 73430-0002 | Form: LIQUID
Manufacturer: Apharm Co., Ltd.
Category: otc | Type: HUMAN OTC DRUG LABEL
Date: 20191102

ACTIVE INGREDIENTS: GLYCERIN 5.021 g/100 g
INACTIVE INGREDIENTS: ALLANTOIN; BUTYLENE GLYCOL

ACTIVE INGREDIENT

glycerin

PURPOSE

dual functionality for brightening and wrinkle improvement certified

Keep out of reach of children

INDICATIONS AND USAGE

1. put 1st and 2nd packs in the pouch and seal them and shake them for 10 seconds

2. sweep the contents down and tear them along the bottom cut line

3. apply mixture to the fact with a sqag-hola and gently remove it from the bottom to the top after 20~30 minutes

4. remove the pack and apply skin product

WARNINGS

1) if there is any abnormal symptom or side effect, such as red spot, swelling and itching when using cosmetlcs or after using due to direct sunlight, consult dermatologists
2) Do not use for wounded areas
3) Precautions for storage and handling
keep out of reach of children, store away from direct sunlight
4) avoid the eye area

INACTIVE INGREDIENT

water, butylene glycol, 1,2-hexanediol, citric acid, etc

DOSAGE AND ADMINISTRATION

For external use only